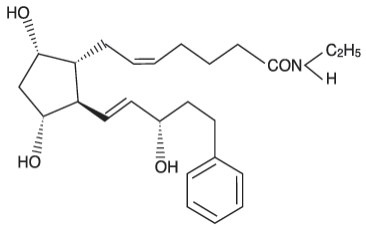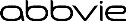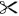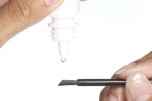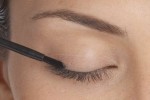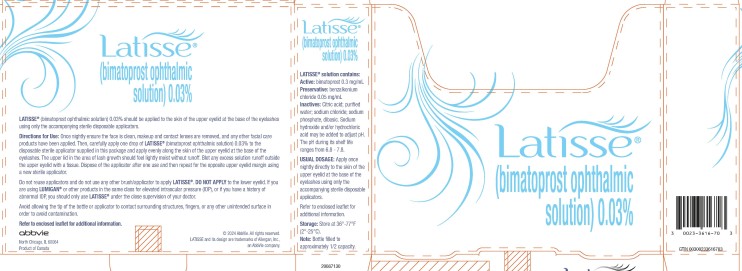 DRUG LABEL: LATISSE
NDC: 0023-3616 | Form: SOLUTION/ DROPS
Manufacturer: Allergan, Inc.
Category: prescription | Type: HUMAN PRESCRIPTION DRUG LABEL
Date: 20240701

ACTIVE INGREDIENTS: BIMATOPROST 0.3 mg/1 mL
INACTIVE INGREDIENTS: BENZALKONIUM CHLORIDE; SODIUM CHLORIDE; SODIUM PHOSPHATE, DIBASIC, UNSPECIFIED FORM; CITRIC ACID MONOHYDRATE; WATER

HIGHLIGHTS OF PRESCRIBING INFORMATION

These highlights do not include all the information needed to use LATISSE safely and effectively. See full prescribing information for LATISSE.
LATISSE® (bimatoprost ophthalmic solution) 0.03%, for topical ophthalmic use
Initial U.S. Approval: 2001

1 INDICATIONS AND USAGE

LATISSE® is a prostaglandin analog, indicated to treat hypotrichosis of the eyelashes by increasing their growth including length, thickness and darkness. (1)

2 DOSAGE AND ADMINISTRATION

Apply nightly directly to the skin of the upper eyelid margin at the base of the eyelashes using the accompanying applicators. Blot any excess solution beyond the eyelid margin. Dispose of the applicator after one use. Repeat for the opposite eyelid margin using a new sterile applicator. (2)

3 DOSAGE FORMS AND STRENGTHS

Ophthalmic solution containing bimatoprost 0.3 mg/mL. (3)

4 CONTRAINDICATIONS

Hypersensitivity. (4)

5 WARNINGS AND PRECAUTIONS

- Concurrent administration of LATISSE® and intraocular pressure (IOP)-lowering prostaglandin analogs in ocular hypertensive patients may decrease the IOP-lowering effect. Patients using these products concomitantly should be closely monitored for changes to their IOP. (5.1)
- Pigmentation of the eyelids and iris may occur. Iris pigmentation is likely to be permanent. (5.2, 5.3)

6 ADVERSE REACTIONS

Most common adverse reactions (incidence approximately 3% to 4%) are eye pruritus, conjunctival hyperemia, and skin hyperpigmentation. (6.1)

To report SUSPECTED ADVERSE REACTIONS, contact AbbVie at 1-800-678-1605 or the FDA at 1-800-FDA-1088 or www.fda.gov/medwatch.

FULL PRESCRIBING INFORMATION

1 INDICATIONS AND USAGE

LATISSE® (bimatoprost ophthalmic solution) 0.03% is indicated to treat hypotrichosis of the eyelashes by increasing their growth including length, thickness and darkness.

2 DOSAGE AND ADMINISTRATION

Ensure the face is clean, makeup and contact lenses are removed. Once nightly, place one drop of LATISSE® (bimatoprost ophthalmic solution) 0.03% on the disposable sterile applicator supplied with the package and apply evenly along the skin of the upper eyelid margin at the base of the eyelashes. The upper lid margin in the area of lash growth should feel lightly moist without runoff. Blot any excess solution runoff outside the upper eyelid margin with a tissue or other absorbent cloth. Dispose of the applicator after one use. Repeat for the opposite eyelid margin using a new sterile applicator.

Do not reuse applicators and do not use any other brush/applicator to apply LATISSE®.

Do not apply to the lower eyelash line [see Warnings and Precautions (5.3, 5.4) and Patient Counseling Information (17)].

Additional applications of LATISSE® will not increase the growth of eyelashes.

Upon discontinuation of treatment, eyelash growth is expected to return to its pre-treatment level.

3 DOSAGE FORMS AND STRENGTHS

Ophthalmic solution containing bimatoprost 0.3 mg/mL.

4 CONTRAINDICATIONS

LATISSE® is contraindicated in patients with hypersensitivity to bimatoprost or to any of the ingredients [see Adverse Reactions (6.2)].

5 WARNINGS AND PRECAUTIONS

5.1 Effects on Intraocular Pressure

Bimatoprost ophthalmic solution (LUMIGAN®) lowers intraocular pressure (IOP) when instilled directly to the eye in patients with elevated IOP. In clinical trials, in patients with or without elevated IOP, LATISSE® lowered IOP, however, the magnitude of the reduction was not cause for clinical concern.

In ocular hypertension studies with LUMIGAN®, it has been shown that exposure of the eye to more than one dose of bimatoprost daily may decrease the intraocular pressure lowering effect. In patients using LUMIGAN® or other prostaglandin analogs for the treatment of elevated intraocular pressure, the concomitant use of LATISSE® may interfere with the desired reduction in IOP. Patients using prostaglandin analogs including LUMIGAN® for IOP reduction should only use LATISSE® after consulting with their physician and should be monitored for changes to their intraocular pressure.

5.2 Iris Pigmentation

Increased iris pigmentation has occurred when bimatoprost solution was administered. Patients should be advised about the potential for increased brown iris pigmentation which is likely to be permanent [see Adverse Reactions (6.2)].

The pigmentation change is due to increased melanin content in the melanocytes rather than to an increase in the number of melanocytes. The long term effects of increased pigmentation are not known. Iris color changes seen with administration of bimatoprost ophthalmic solution may not be noticeable for several months to years. Typically, the brown pigmentation around the pupil spreads concentrically towards the periphery of the iris and the entire iris or parts of the iris become more brownish. Neither nevi nor freckles of the iris appear to be affected by treatment. Treatment with LATISSE® solution can be continued in patients who develop noticeably increased iris pigmentation.

5.3 Lid Pigmentation

Bimatoprost has been reported to cause pigment changes (darkening) to periorbital pigmented tissues and eyelashes. The pigmentation is expected to increase as long as bimatoprost is administered, but has been reported to be reversible upon discontinuation of bimatoprost in most patients.

5.4 Hair Growth Outside the Treatment Area

There is the potential for hair growth to occur in areas where LATISSE® solution comes in repeated contact with the skin surface. It is important to apply LATISSE® only to the skin of the upper eyelid margin at the base of the eyelashes using the accompanying sterile applicators, and to carefully blot any excess LATISSE® from the eyelid margin to avoid it running onto the cheek or other skin areas.

5.5 Intraocular Inflammation

LATISSE® solution should be used with caution in patients with active intraocular inflammation (e.g., uveitis) because the inflammation may be exacerbated.

5.6 Macular Edema

Macular edema, including cystoid macular edema, has been reported during treatment with bimatoprost ophthalmic solution (LUMIGAN®) for elevated IOP. LATISSE® should be used with caution in aphakic patients, in pseudophakic patients with a torn posterior lens capsule, or in patients with known risk factors for macular edema.

5.7 Contamination of LATISSE® or Applicators

The LATISSE® bottle must be kept intact during use. It is important to use LATISSE® solution as instructed, by placing one drop on the single-use-per-eye applicator. The bottle tip should not be allowed to contact any other surface since it could become contaminated. The accompanying sterile applicators should only be used on one eye and then discarded since reuse of applicators increases the potential for contamination and infections. There have been reports of bacterial keratitis associated with the use of multiple-dose containers of topical ophthalmic products [see Patient Counseling Information (17)].

5.8 Use with Contact Lenses

LATISSE® contains benzalkonium chloride, which may be absorbed by and cause discoloration of soft contact lenses. Contact lenses should be removed prior to application of solution and may be reinserted 15 minutes following its administration.

6 ADVERSE REACTIONS

The following adverse reactions are described elsewhere in the labeling:

- Effects on Intraocular Pressure [see Warnings and Precautions (5.1)]
- Iris Pigmentation [see Warnings and Precautions (5.2)]
- Lid Pigmentation [see Warnings and Precautions (5.3)]
- Hair Growth Outside the Treatment Area [see Warnings and Precautions (5.4)]
- Intraocular Inflammation [see Warnings and Precautions (5.5)]
- Macular Edema [see Warnings and Precautions (5.6)]
- Hypersensitivity [see Contraindications (4)]

6.1 Clinical Trial Experience

Because clinical trials are conducted under widely varying conditions, adverse reaction rates observed in the clinical trials of a drug cannot be directly compared to rates in the clinical trials of another drug and may not reflect the rates observed in practice.

The following information is based on clinical trial results from a multicenter, double-masked, randomized, vehicle-controlled, parallel study including 278 adult patients for four months of treatment.

The most frequently reported adverse reactions were eye pruritus, conjunctival hyperemia, skin hyperpigmentation, ocular irritation, dry eye symptoms, and periorbital erythema. These reactions occurred in less than 4% of patients. Additional adverse reactions seen in clinical trials experience include foreign body sensation, hair growth abnormal, and iris hyperpigmentation.

Additional adverse reactions reported with bimatoprost ophthalmic solution (LUMIGAN®) for the reduction of intraocular pressure include, ocular dryness, visual disturbance, ocular burning, eye pain, blepharitis, cataract, superficial punctate keratitis, eye discharge, tearing, photophobia, allergic conjunctivitis, asthenopia, conjunctival edema, iritis, infections (primarily colds and upper respiratory tract infections), headaches, and asthenia.

6.2 Postmarketing Experience

The following adverse reactions have been identified during postapproval use of LATISSE®. Because these reactions are reported voluntarily from a population of uncertain size, it is not always possible to reliably estimate their frequency or establish a causal relationship to drug exposure. The reactions include dry skin of the eyelid and/or periocular area, eye swelling, eyelid edema, hordeolum, hypersensitivity (local allergic reactions), lacrimation increased, madarosis and trichorrhexis (temporary loss of a few lashes to loss of sections of eyelashes, and temporary eyelash breakage, respectively), periorbital and lid changes associated with periorbital fat atrophy and skin tightness resulting in deepening of eyelid sulcus and eyelid ptosis, rash (including macular and erythematous), skin discoloration (periorbital), skin exfoliation of the eyelid and/or periorbital area, trichiasis, and vision blurred.

8 USE IN SPECIFIC POPULATIONS

8.1 Pregnancy

Risk Summary

There are no adequate and well-controlled studies of LATISSE® (bimatoprost ophthalmic solution) 0.03% administration in pregnant women. There is no increase in the risk of major birth defects or miscarriages based on bimatoprost postmarketing experience.

In embryofetal development studies, administration of bimatoprost to pregnant mice and rats during organogenesis resulted in abortion and early delivery at oral doses at least 33 times (mice) or 94 times (rats) the human exposure following topical ophthalmic administration of bimatoprost 0.03% to the cornea or conjunctival sac bilaterally once daily, based on the area under the curve (AUC). These adverse effects were not observed at 2.6 times (mice) and 47 times (rats) the human exposure following topical ophthalmic administration of bimatoprost 0.03% to the cornea or conjunctival sac bilaterally once daily, based on AUC.

In pre/postnatal development studies, administration of bimatoprost to pregnant rats from organogenesis to the end of lactation resulted in reduced gestation length and fetal body weight, and increased fetal and pup mortality at oral doses at least 41 times the human systemic exposure following topical ophthalmic administration of bimatoprost 0.03% to the cornea or conjunctival sac bilaterally once daily, based on AUC. No adverse effects were observed in rat offspring at exposures estimated at 14 times the human exposure following topical ophthalmic administration of bimatoprost 0.03% to the cornea or conjunctival sac bilaterally once daily, based on AUC.

Because animal reproductive studies are not always predictive of human response LATISSE® 0.03% should be administered during pregnancy only if the potential benefit justifies the potential risk to the fetus.

Data

Animal Data

In an embryofetal development rat study, abortion was observed in pregnant rats administered bimatoprost orally during organogenesis at 0.6 mg/kg/day (94 times the human systemic exposure following topical ophthalmic administration of bimatoprost 0.03% to the cornea or conjunctival sac bilaterally once daily, based on AUC). The No Observed Adverse Effect Level (NOAEL) for abortion was 0.3 mg/kg/day (estimated at 47 times the human systemic exposure following topical ophthalmic administration of bimatoprost 0.03% to the cornea or conjunctival sac bilaterally once daily based on AUC). No abnormalities were observed in rat fetuses at doses up to 0.6 mg/kg/day.

In an embryofetal development mouse study, abortion and early delivery were observed in pregnant mice administered bimatoprost orally during organogenesis at doses greater than or equal to 0.3 mg/kg/day (33 times the human systemic exposure following topical ophthalmic administration of bimatoprost 0.03% to the cornea or conjunctival sac bilaterally once daily, based on AUC). The NOAEL for abortion and early delivery was 0.1 mg/kg/day (2.6 times the human systemic exposure following topical ophthalmic administration of bimatoprost 0.03% to the cornea or conjunctival sac bilaterally once daily, based on AUC). No abnormalities were observed in mouse fetuses at doses up to 0.6 mg/kg/day (72 times the human systemic exposure following topical ophthalmic administration of bimatoprost 0.03% to the cornea or conjunctival sac bilaterally once daily, based on AUC).

In a pre/postnatal development study, treatment of pregnant rats with bimatoprost orally from gestation day 7 to lactation day 20 resulted in reduced gestation length, increased late resorptions, fetal deaths, and postnatal pup mortality, and reduced pup body weight at doses greater than or equal to 0.3 mg/kg/day. These effects were observed at exposures at least 41 times the human systemic exposure following topical ophthalmic administration of bimatoprost 0.03% to the cornea or conjunctival sac bilaterally once daily, based on AUC. The NOAEL for postnatal development and mating performance of the offspring was 0.1 mg/kg/day (estimated at 14 times the human systemic exposure following topical ophthalmic administration of bimatoprost 0.03% to the cornea or conjunctival sac bilaterally once daily, based on AUC).

8.2 Lactation

Risk Summary

It is not known whether topical ocular treatment with LATISSE® 0.03% could result in sufficient systemic absorption to produce detectable quantities in human milk. In animal studies, bimatoprost has been shown to be present in breast milk of lactating rats at an intravenous dose (i.e., 1 mg/kg) 324 times the recommended human ophthalmic dose (on a mg/m^2 basis), however no animal data is available at clinically relevant doses.

The developmental and health benefits of breastfeeding should be considered along with the mother’s clinical need for LATISSE® 0.03% and any potential adverse effects on the breastfed child from LATISSE® 0.03%.

8.4 Pediatric Use

Use of LATISSE® was evaluated in a sixteen-week double-masked, randomized, vehicle-controlled study conducted in pediatric patients who were post-chemotherapy or had alopecia areata, and adolescents who had hypotrichosis with no associated medical condition. No new safety issues were observed. The results of the Global Eyelash Assessment (GEA) are provided in Table 1.

Table 1. Number (%) of subjects with at least a 1-grade increase from baseline at month 4 in Global Eyelash Assessment
 | Age Range (years) | LATISSE® | Vehicle | Difference (95% CI)
Adolescents with hypotrichosis (N=40) | 15 - 17 | 19/26 (73%) | 1/14 (7%) | 66% (44%, 88%)
Post Chemotherapy Pediatric Patients (N=16) | 5 - 17 | 11/13 (85%) | 3/3 (100%) | -15% (-35%, 4%)
Alopecia Areata Pediatric Patients (N=15) | 5 - 17 | 4/9 (44%) | 2/6 (33%) | 11% (-39%, 61%)

8.5 Geriatric Use

No overall clinical differences in safety or effectiveness have been observed between elderly and other adult patients.

11 DESCRIPTION

LATISSE® (bimatoprost ophthalmic solution) 0.03% is a synthetic prostaglandin analog. Its chemical name is (Z)-7-[(1R,2R,3R,5S)-3,5-Dihydroxy-2-[(1E,3S)-3-hydroxy-5-phenyl-1-pentenyl]cyclopentyl]-N-ethyl-5-heptenamide, and its molecular weight is 415.58. Its molecular formula is C25H37NO4. Its chemical structure is:

Bimatoprost is a powder, which is very soluble in ethyl alcohol and methyl alcohol and slightly soluble in water. LATISSE® is a clear, isotonic, colorless, sterile ophthalmic solution with an osmolality of approximately 290 mOsmol/kg.

Contains: Active: bimatoprost 0.3 mg/mL; Preservative: benzalkonium chloride 0.05 mg/mL; Inactives: sodium chloride; sodium phosphate, dibasic; citric acid; and purified water. Sodium hydroxide and/or hydrochloric acid may be added to adjust pH. The pH during its shelf life ranges from 6.8 - 7.8.

12 CLINICAL PHARMACOLOGY

12.1 Mechanism of Action

Bimatoprost is a structural prostaglandin analog. Although the precise mechanism of action is unknown, the growth of eyelashes is believed to occur by increasing the percent of hairs in, and the duration of the anagen or growth phase.

12.3 Pharmacokinetics

Absorption

After one drop of bimatoprost ophthalmic solution 0.03% was administered once daily into both eyes (cornea and/or conjunctival sac) of 15 healthy subjects for two weeks, blood concentrations peaked within 10 minutes after dosing and were below the lower limit of detection (0.025 ng/mL) in most subjects within 1.5 hours after dosing. Mean Cmax and AUC0-24hr values were similar on days 7 and 14 at approximately 0.08 ng/mL and 0.09 ng●hr/mL, respectively, indicating that steady state was reached during the first week of ocular dosing. There was no significant systemic drug accumulation over time.

Distribution

Bimatoprost is moderately distributed into body tissues with a steady-state volume of distribution of 0.67 L/kg. In human blood, bimatoprost resides mainly in the plasma. Approximately 12% of bimatoprost remains unbound in human plasma.

Elimination

Metabolism

Bimatoprost is the major circulating species in the blood once it reaches the systemic circulation. Bimatoprost then undergoes oxidation, N-deethylation, and glucuronidation to form a diverse variety of metabolites.

Excretion

Following an intravenous dose of radiolabeled bimatoprost (3.12 mcg/kg) to six healthy subjects, the maximum blood concentration of unchanged drug was 12.2 ng/mL and decreased rapidly with an elimination half-life of approximately 45 minutes. The total blood clearance of bimatoprost was 1.5 L/hr/kg. Up to 67% of the administered dose was excreted in the urine while 25% of the dose was recovered in the feces.

13 NONCLINICAL TOXICOLOGY

13.1 Carcinogenesis, Mutagenesis, Impairment of Fertility

Carcinogenesis

Bimatoprost was not carcinogenic in either mice or rats when administered by oral gavage for 104 weeks at doses up to 2 mg/kg/day and 1 mg/kg/day, respectively (192 and 291 times the human systemic exposure following topical ophthalmic administration of bimatoprost 0.03% to the cornea or conjunctival sac bilaterally once daily based on blood AUC levels).

Mutagenesis

Bimatoprost was not mutagenic or clastogenic in the Ames test, in the mouse lymphoma test, or in the in vivo mouse micronucleus tests.

Impairment of Fertility

Bimatoprost did not impair fertility in male or female rats up to doses of 0.6 mg/kg/day (103 times the human systemic exposure following topical ophthalmic administration of bimatoprost 0.03% to the cornea or conjunctival sac bilaterally once daily based on blood AUC levels).

14 CLINICAL STUDIES

LATISSE® solution was evaluated for its effect on overall eyelash prominence in a multicenter, double-masked, randomized, vehicle-controlled, parallel study including 278 adult patients for four months of treatment. The primary efficacy endpoint in this study was an increase in overall eyelash prominence as measured by at least a 1-grade increase on the 4-point Global Eyelash Assessment (GEA) scale, from baseline to the end of the treatment period (week 16). LATISSE® was more effective than vehicle as measured by the GEA score, with statistically significant differences seen at 8-week, 12-week, and 16-week (primary endpoint) treatment durations.

Table 2. Number (%) of subjects with at least a 1-grade increase from baseline in Global Eyelash Assessment (Primary Efficacy Endpoint – Week 16)
Week | LATISSE® N=137 N (%) | Vehicle N=141 N (%)
1 | 7 (5%) | 3 (2%)
4 | 20 (15%) | 11 (8%)
8 | 69 (50%) | 21 (15%)
12 | 95 (69%) | 28 (20%)
16 | 107 (78%) | 26 (18%)
20 | 103 (79%) | 27 (21%)

In this study, patients were also evaluated for the effect of LATISSE® solution on the length, thickness and darkness of their eyelashes. Improvements from baseline in eyelash growth as measured by digital image analysis assessing eyelash length, fullness/thickness, and darkness were statistically significantly more pronounced in the bimatoprost group at weeks 8, 12, and 16.

Table 3
Efficacy endpoint at Week 16 (Mean Change from Baseline) | LATISSE® | Vehicle
Eyelash growth (length) (mm; % increase) | N=137 1.4; 25% | N=141 0.1; 2%
Fullness/thickness (mm^2; % increase) | N=136 0.7; 106% | N=140 0.1; 12%
Eyelash darkness (intensity*; % increase in darkness) | N=135 -20.2; -18% | N=138 -3.6; -3%

* a negative value is representative of eyelash darkening

After the 16-week treatment period, a 4-week post-treatment period followed during which the effects of bimatoprost started to return toward baseline. The effect on eyelash growth is expected to abate following longer term discontinuation.

16 HOW SUPPLIED/STORAGE AND HANDLING

LATISSE® (bimatoprost ophthalmic solution) 0.03% is supplied sterile in opaque white low-density polyethylene dispenser bottles and tips with turquoise polystyrene caps accompanied by sterile, disposable applicators:

3 mL in a 5 mL bottle with 70 applicators NDC 0023-3616-70
5 mL in a 5 mL bottle with 140 applicators NDC 0023-3616-05

Storage: Store at 2º to 25ºC (36º to 77ºF).

17 PATIENT COUNSELING INFORMATION

Advise the patient to read the FDA-approved patient labeling (Patient Information).

Nightly Application

Inform patients that LATISSE® (bimatoprost ophthalmic solution) should be applied every night using only the accompanying sterile applicators. They should start by ensuring their face is clean, all makeup is removed, and their contact lenses removed (if applicable). Then, carefully place one drop of LATISSE® solution on the disposable sterile applicator and brush cautiously along the skin of the upper eyelid margin at the base of the eyelashes. If any LATISSE® solution gets into the eye proper, it will not cause harm. The eye should not be rinsed.

Additional applications of LATISSE® will not increase the growth of eyelashes.

Inform patients not to apply to the lower eyelash line. Any excess solution outside the upper eyelid margin should be blotted with a tissue or other absorbent material.

The onset of effect is gradual but is not significant in the majority of patients until 2 months. Counsel patients that the effect is not permanent and can be expected to gradually return to the original level upon discontinuation of treatment with LATISSE®.

Handling the Bottle and Applicator

Instruct patients that the LATISSE® bottle must be maintained intact and to avoid allowing the tip of the bottle or applicator to contact surrounding structures, fingers, or any other unintended surface in order to avoid contamination of the bottle or applicator by common bacteria known to cause ocular infections. Instruct patients to only use the applicator supplied with the product once and then discard since reuse could result in using a contaminated applicator. Serious infections may result from using contaminated solutions or applicators.

Potential for Intraocular Pressure Effects

LATISSE® may lower intraocular pressure although not to a level that will cause clinical harm.

In patients using LUMIGAN® or other prostaglandin analogs for the treatment of elevated intraocular pressure, the concomitant use of LATISSE® may interfere with the desired reduction in IOP. Patients using prostaglandin analogs for IOP reduction should only use LATISSE® after consulting with their physician.

Potential for Eyelid Skin Darkening

Inform patients about the possibility of eyelid skin darkening, which may be reversible after discontinuation of LATISSE®.

Potential for Iris Darkening

Advise patients about the potential for increased brown iris pigmentation which is likely to be permanent. Increased iris pigmentation has occurred when bimatoprost solution was administered.

Potential for Unexpected Hair Growth or Eyelash Changes

Inform patients of the possibility of hair growth occurring outside of the target treatment area if LATISSE® repeatedly touches the same area of skin outside the treatment area. They should also be informed of the possibility of disparity between eyes in length, thickness, pigmentation, number of eyelashes or vellus hairs, and/or direction of eyelash growth. Eyelash changes are likely reversible upon discontinuation of treatment.

When to Seek Physician Advice

Advise patients that if they develop a new ocular condition (e.g., trauma or infection), experience a sudden decrease in visual acuity, have ocular surgery, or develop any ocular reactions, particularly conjunctivitis and eyelid reactions, they should immediately seek their physician’s advice concerning the continued use of LATISSE®. Patients on IOP-lowering medications should not use LATISSE® without prior consultation with their physician.

Contact Lens Use

Advise patients that LATISSE® solution contains benzalkonium chloride, which may be absorbed by and cause discoloration of soft contact lenses. Contact lenses should be removed prior to application of LATISSE® and may be reinserted 15 minutes following its administration.

Distributed by:
AbbVie Inc.
North Chicago, IL 60064

© 2024 AbbVie. All rights reserved.
LATISSE and its design are trademarks of Allergan, Inc., an AbbVie company.

v3.0USPI3616

------Cut---Here--- -------------------------------------------------------------------------------------------------------------

FDA-approved Patient Labeling

PATIENT INFORMATION

LATISSE® [la teece]
(bimatoprost ophthalmic solution) 0.03%
Read the Patient Information that comes with LATISSE® before you start using it and each time you get a refill. There may be new information. This leaflet does not take the place of talking with your physician about your treatment.

What is hypotrichosis of the eyelashes?

Hypotrichosis is another name for having inadequate or not enough eyelashes.

What is LATISSE® solution?

LATISSE® solution is a prescription treatment for hypotrichosis used to grow eyelashes, making them longer, thicker and darker.

Who should NOT take LATISSE®?

Do not use LATISSE® solution if you are allergic to one of its ingredients.

Are there any special warnings associated with LATISSE® use?

LATISSE® solution is intended for use on the skin of the upper eyelid margins at the base of the eyelashes. Refer to Illustration 2 below. DO NOT APPLY to the lower eyelid. If you are using LUMIGAN® or other products in the same class for elevated intraocular pressure (IOP), or if you have a history of abnormal IOP, you should only use LATISSE® under the close supervision of your physician.

LATISSE® use may cause darkening of the eyelid skin which may be reversible. LATISSE® use may also cause increased brown pigmentation of the colored part of the eye which is likely to be permanent.

It is possible for hair growth to occur in other areas of your skin that LATISSE® frequently touches. Any excess solution outside the upper eyelid margin should be blotted with a tissue or other absorbent material to reduce the chance of this from happening. It is also possible for a difference in eyelash length, thickness, fullness, pigmentation, number of eyelash hairs, and/or direction of eyelash growth to occur between eyes. These differences, should they occur, will usually go away if you stop using LATISSE®.

Who should I tell that I am using LATISSE®?

You should tell your physician you are using LATISSE® especially if you have a history of eye pressure problems.

You should also tell anyone conducting an eye pressure screening that you are using LATISSE®.

What should I do if I get LATISSE® in my eye?

LATISSE® solution is an ophthalmic drug product. LATISSE® is not expected to cause harm if it gets into the eye proper. Do not attempt to rinse your eye in this situation.

What are the possible side effects of LATISSE®?

The most common side effects after using LATISSE® solution are an itching sensation in the eyes and/or eye redness. This was reported in approximately 4% of patients. LATISSE® solution may cause other less common side effects which typically occur on the skin close to where LATISSE® is applied, or in the eyes. These include skin darkening, eye irritation, dryness of the eyes, and redness of the eyelids.

If you develop a new ocular condition (e.g., trauma or infection), experience a sudden decrease in visual acuity, have ocular surgery, or develop any ocular reactions, particularly conjunctivitis and eyelid reactions, you should immediately seek your physician’s advice concerning the continued use of LATISSE® solution.

What happens if I stop using LATISSE®?

If you stop using LATISSE®, your eyelashes are expected to return to their previous appearance over several weeks to months.

Any eyelid skin darkening is expected to reverse after several weeks to months.

Any darkening of the colored part of the eye known as the iris is NOT expected to reverse and is likely permanent.

How do I use LATISSE®?

The recommended dosage is one application nightly to the skin of the upper eyelid margin at the base of the eyelashes only.

Once nightly, start by ensuring your face is clean, makeup and contact lenses are removed. Remove an applicator from its tray. Then, holding the sterile applicator horizontally, place one drop of LATISSE® on the area of the applicator closest to the tip but not on the tip (see Illustration 1). Then immediately draw the applicator carefully across the skin of the upper eyelid margin at the base of the eyelashes (where the eyelashes meet the skin) going from the inner part of your lash line to the outer part (see Illustration 2). Blot any excess solution beyond the eyelid margin. Dispose of the applicator after one use.

Repeat for the opposite upper eyelid margin using a new sterile applicator. This helps minimize any potential for contamination from one eyelid to another.

Illustration 1

Illustration 2

DO NOT APPLY in your eye or to the lower lid. ONLY use the sterile applicators supplied with LATISSE® to apply the product. If you miss a dose, don’t try to “catch up.” Just apply LATISSE® solution the next evening. Fifty percent of patients treated with LATISSE® in a clinical study saw significant improvement by 2 months after starting treatment.

If any LATISSE® solution gets into the eye proper, it is not expected to cause harm. The eye should not be rinsed.

Don’t allow the tip of the bottle or applicator to contact surrounding structures, fingers, or any other unintended surface in order to avoid contamination by common bacteria known to cause infections.

Contact lenses should be removed prior to application of LATISSE® and may be reinserted 15 minutes following its administration.

Use of LATISSE® more than once a day will not increase the growth of eyelashes more than use once a day.

Store LATISSE® solution at 36o to 77oF (2o to 25oC).

General Information about LATISSE®
Prescription treatments are sometimes prescribed for conditions that are not mentioned in patient information leaflets. Do not use LATISSE® solution for a condition for which it was not prescribed. Do not give LATISSE® to other people. It may not be appropriate for them to use.

This leaflet summarizes the most important information about LATISSE® solution. If you would like more information, talk with your physician. You can also call AbbVie’s product information department at 1-800-678-1605.

What are the ingredients in LATISSE®?

Active ingredient: bimatoprost
Inactive ingredients: benzalkonium chloride; sodium chloride; sodium phosphate, dibasic; citric acid; and purified water. Sodium hydroxide and/or hydrochloric acid may be added to adjust pH. The pH during its shelf life ranges from 6.8 - 7.8.

Distributed by:
AbbVie Inc.
North Chicago, IL 60064

© 2024 AbbVie. All rights reserved.
LATISSE and its design are trademarks of Allergan, Inc., an AbbVie company.

v2.0PPI3616

PACKAGE LABEL

PRINCIPAL DISPLAY PANEL

NDC 0023-3616-70
Latisse®
(bimatoprost ophthalmic
solution) 0.03%
Rx only
abbvie
Contents:
One 3 mL bottle of sterile solution
70 disposable applicators